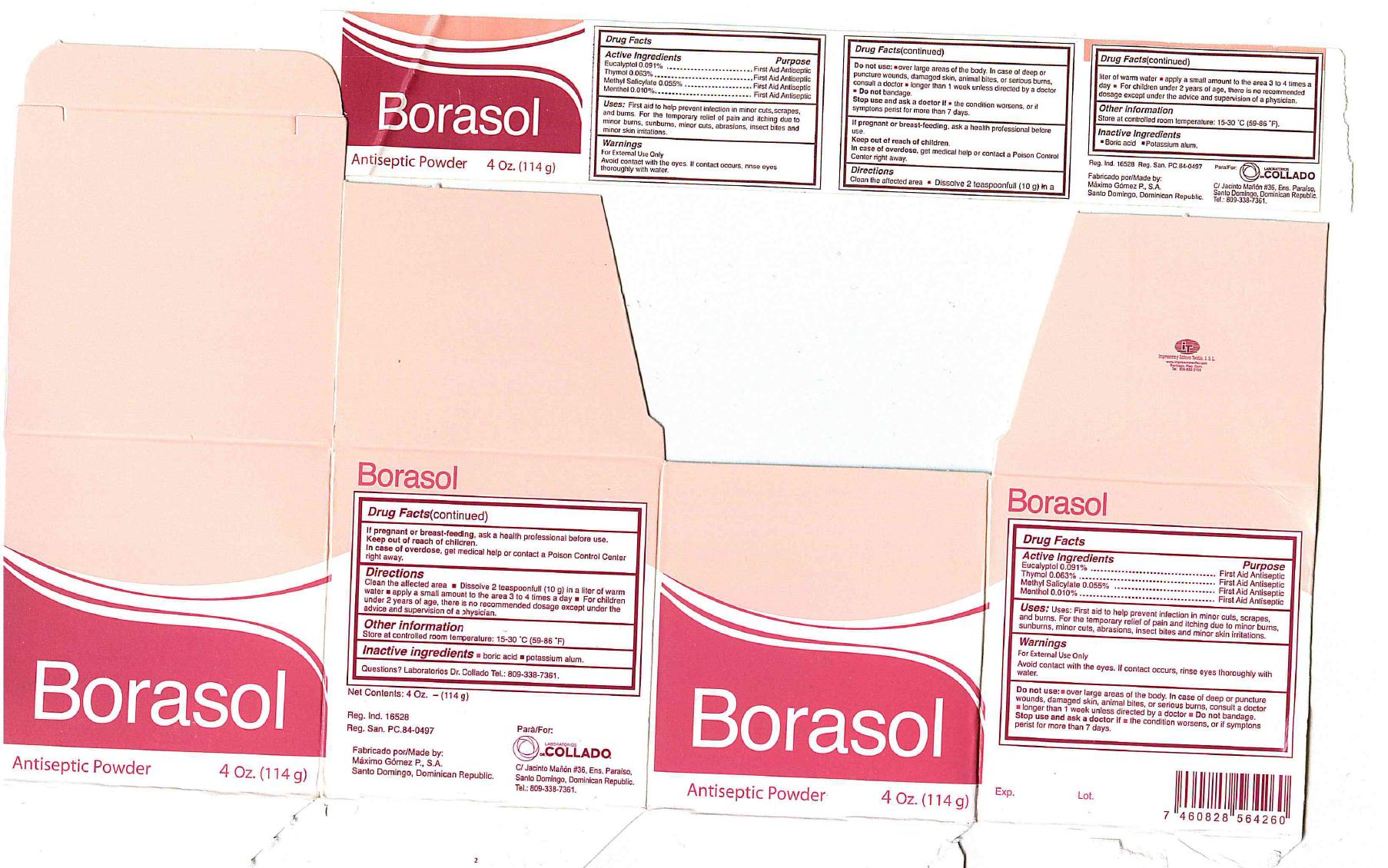 DRUG LABEL: Borasol
NDC: 42333-100 | Form: POWDER
Manufacturer: Laboratorios Dr. Collado, C x A.
Category: otc | Type: HUMAN OTC DRUG LABEL
Date: 20130520

ACTIVE INGREDIENTS: EUCALYPTOL 0.091 g/100 g; THYMOL 0.063 g/100 g; METHYL SALICYLATE 0.055 g/100 g; MENTHOL 0.01 g/100 g
INACTIVE INGREDIENTS: BORIC ACID; POTASSIUM ALUM

Drug Facts

Active Ingredients Purpose

Eucalyptol 0.091% First Aid Antiseptic
Thymol 0.063% First Aid Antiseptic
Methyl Salicylate 0.055% First Aid Antiseptic
Menthol 0.010% First Aid Antiseptic

Purpose

First Aid Antiseptic

Warnings

For external use only

Avoid contact with the eyes. If contact occurs, rinse eyes thoroughly with water.

Do not use:

- over large areas of the body. In case of deep or puncture wounds, damaged skin, animal bites, or serious burns, consult a doctor
- longer than 1 week unless directed by a doctor
- Do not bandage.

Stop use and ask a doctor if

- the condition worsens, or if symptoms persist for more than 7 days

PREGNANCY OR BREAST FEEDING

If pregnant or breast-feeding, ask a health professional before use

Keep out of reach of children.

In case of overdose, get medical help or contact a Poison Control Center right away.

Directions

- Clean the affected area
- Dissolve 2 teasponnfull (10g) in a liter of warm water
- apply a small amount to the area 3 to 4 times a day
- For children under 2 years of agea, there is no recommended dosage except under the advice and supervision of a physician

INDICATIONS AND USAGE

Uses:First aid to help prevent infection in minor cuts, scrapes, and burns. For the temporary relief of pain and itching due to minor burns, sunburns, minor cuts, abrasions, insect bites and minor skin irritations.

Other information

Store at controlled room temperature: 15-30 degrees C (59-86 degrees F)

Inactive ingredients

boric acid, potassium alum

Questions?Laboratorios Dr. Collado Tel: 809-338-7361